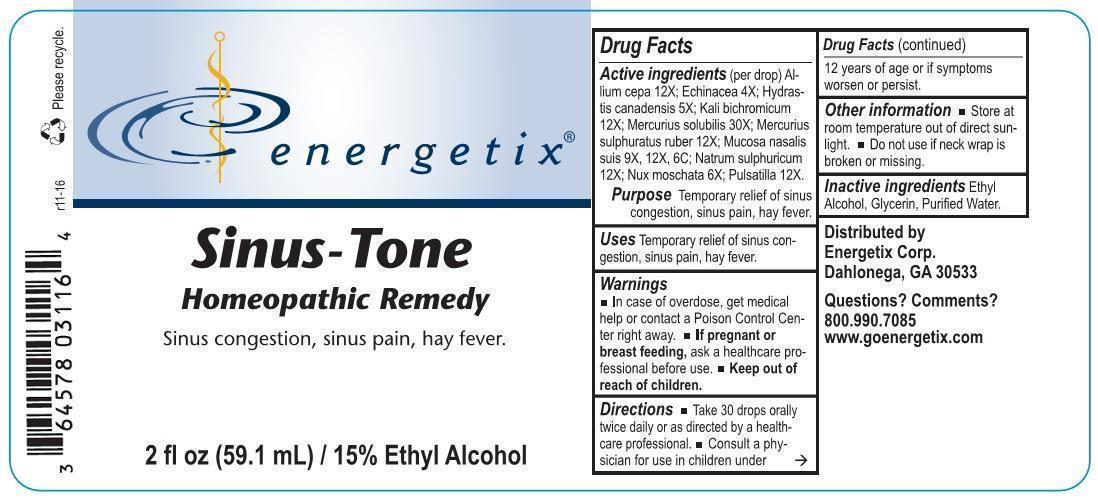 DRUG LABEL: Sinus Tone
NDC: 64578-0129 | Form: LIQUID
Manufacturer: Energetix Corp
Category: homeopathic | Type: HUMAN OTC DRUG LABEL
Date: 20170103

ACTIVE INGREDIENTS: ONION 12 [hp_X]/1 mL; ECHINACEA ANGUSTIFOLIA 4 [hp_X]/1 mL; GOLDENSEAL 5 [hp_X]/1 mL; POTASSIUM DICHROMATE 12 [hp_X]/1 mL; MERCURIUS SOLUBILIS 30 [hp_X]/1 mL; MERCURIC SULFIDE 12 [hp_X]/1 mL; SUS SCROFA NASAL MUCOSA 9 [hp_X]/1 mL; SODIUM SULFATE 12 [hp_X]/1 mL; NUTMEG 6 [hp_X]/1 mL; PULSATILLA VULGARIS 12 [hp_X]/1 mL
INACTIVE INGREDIENTS: WATER; GLYCERIN; ALCOHOL

Drug Facts:

Active ingredients (per drop)

Allium cepa 12X, Echinacea 4X, Hydrastis canadensis 5X, Kali bichromicum 12X, Mercurius solubilis 30X, Mercurius sulphuratus ruber 12X, Mucosa nasalis suis 9X, 12X, 6C, Natrum sulphuricum 12X, Nux moschata 6X, Pulsatilla 12X.

Purpose

Temporary relief of sinus congestion, sinus pain, hay fever.

Uses

Temporary relief of sinus congestion, sinus pain, hay fever.

Warnings

- In case of overdose, get medical help or contact a Poison Control Center right away.
- If pregnant or breast feeding, ask a healthcare professional before use.
- Keep out of reach of children.

Keep out of reach of children.

Directions

- Take 30 drops orally twice daily or as directed by a healthcare professional.
- Consult a physician for use in children under 12 years of age or if symptoms worsen or persist.

Other information

- Store at room temperature out of direct sunlight.
- Do not use if neck wrap is broken or missing.

Inactive ingredients

Ethyl Alcohol, Glycerin, Purified Water.

QUESTIONS

Distributed by

Energetix Corp.

Dahlonega, GA 30533

Questions? Comments?

800.990.7085

www.goenergetix.com

PURPOSE

Sinus congestion, sinus pain, hay fever.

PACKAGE LABEL

energetix

Sinus-Tone

Homeopathic Remedy

Sinus congestion, sinus pain, hay fever.

2 fl oz (59.1 mL) / 15% Ethyl Alcohol